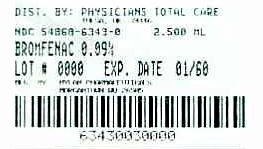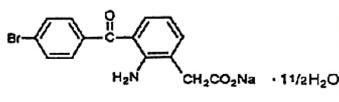 DRUG LABEL: Bromfenac
NDC: 54868-6343 | Form: SOLUTION/ DROPS
Manufacturer: Physicians Total Care, Inc.
Category: prescription | Type: HUMAN PRESCRIPTION DRUG LABEL
Date: 20120417

ACTIVE INGREDIENTS: Bromfenac sodium 1.035 mg/1 mL
INACTIVE INGREDIENTS: Benzalkonium chloride 0.05 mg/1 mL; Boric acid 11 mg/1 mL; edetate disodium 0.2 mg/1 mL; polysorbate 80 1.5 mg/1 mL; povidone 20 mg/1 mL; sodium borate 11 mg/1 mL; sodium sulfite 2 mg/1 mL; sodium hydroxide; water

Bromfenac Ophthlamic Solution

STERILE

DESCRIPTION

Bromfenac ophthalmic solution 0.09% is a sterile, topical, nonsteroidal anti-inflammatory drug (NSAID) for ophthalmic use. Each mL of bromfenac ophthalmic solution contains 1.035 mg bromfenac sodium (equivalent to 0.9 mg bromfenac free acid). Bromfenac sodium is designated chemically as sodium 2-amino-3-(4-bromobenzoyl) phenylacetate sesquihydrate, with an empirical formula of C15H11BrNNaO3 • 1 1/2 H2O. The structural formula of bromfenac sodium is:

Bromfenac sodium is a yellow to orange crystalline powder. The molecular weight of bromfenac sodium is 383.17. Bromfenac ophthalmic solution is supplied as a sterile aqueous 0.09% solution, with a pH of 8.3. The osmolality of bromfenac ophthalmic solution is approximately 300 mOsmol/kg. Each mL of bromfenac ophthalmic solution contains: Active: bromfenac sodium hydrate 0.1035%. Inactives: benzalkonium chloride (0.05 mg/mL), boric acid, disodium edetate (0.2 mg/mL), polysorbate 80 (1.5 mg/mL), povidone (20 mg/mL), sodium borate, sodium sulfite anhydrous (2 mg/mL), sodium hydroxide to adjust the pH, and water for injection, USP.

Clinical Pharmacology

Mechanism of Action

Bromfenac is a nonsteroidal anti-inflammatory drug (NSAID) that has anti-inflammatory activity.The mechanism of its action is thought to be due to its ability to block prostaglandin synthesis by inhibiting cyclooxygenase 1 and 2.

Prostaglandins have been shown in many animal models to be mediators of certain kinds of intraocular inflammation. In studies performed in animal eyes, prostaglandins have been shown to produce disruption of the blood-aqueous humor barrier, vasodilation, increased vascular permeability, leukocytosis, and increased intraocular pressure.

Pharmacokinetics

The plasma concentration of bromfenac following ocular administration of bromfenac ophthalmic solution 0.09% in humans is unknown. Based on the maximum proposed dose of one drop to each eye (0.09mg) and PK information from other routes of administration, the systemic concentration of bromfenac is estimated to be below the limit of quantification (50 ng/mL) at steady-state in humans.

Clinical Trials

Clinical efficacy was evaluated in two randomized, double-masked, vehicle-controlled U.S. trials in which subjects with a summed ocular inflammation score ≥3 after cataract surgery were assigned to bromfenac ophthalmic solution or vehicle in a 2:1 ratio following surgery. One drop of bromfenac ophthalmic solution or vehicle was self-instilled in the study eye twice a day for 14 days, beginning the day after surgery. The primary endpoint was reduction of ocular inflammation (to trace inflammation or clearing) assessed 14 days post-surgery using a slit lamp binocular microscope. In the intent-to-treat analyses of both studies, a significant effect of bromfenac ophthalmic solution on ocular inflammation after cataract surgery was demonstrated (62 to 66% vs. 40 to 48%). An additional efficacy end point was the time required for resolution of ocular pain in subjects who reported pain. Overall, only 20% of the patients undergoing cataract surgery in these trials had pain on the first day after surgery. In these patients, the bromfenac ophthalmic solution group demonstrated a statistically significant difference in median time to resolution of ocular pain of 2 days compared to 4 days for patients receiving vehicle.

Indications and Usage

Bromfenac ophthalmic solution is indicated for the treatment of postoperative inflammation and the reduction of ocular pain in patients who have undergone cataract extraction.

Contraindications

Bromfenac ophthalmic solution is contraindicated in patients with known hypersensitivity to any ingredient in the formulation.

Warnings

Contains sodium sulfite, a sulfite that may cause allergic-type reactions including anaphylactic symptoms and life-threatening or less severe asthmatic episodes in certain susceptible people. The overall prevalence of sulfite sensitivity in the general population is unknown and probably low. Sulfite sensitivity is seen more frequently in asthmatic than in nonasthmatic people.

There is the potential for cross-sensitivity to acetylsalicylic acid, phenylacetic acid derivatives, and other NSAIDs. Therefore, caution should be used when treating individuals who have previously exhibited sensitivities to these drugs.

With some NSAIDs, there exists the potential for increased bleeding time due to interference with platelet aggregation. There have been reports that ocularly applied NSAIDs may cause increased bleeding of ocular tissues (including hyphemas) in conjunction with ocular surgery.

Precautions

General

All topical nonsteroidal anti-inflammatory drugs (NSAIDs) may slow or delay healing. Topical corticosteroids are also known to slow or delay healing. Concomitant use of topical NSAIDs and topical steroids may increase the potential for healing problems.

Use of topical NSAIDs may result in keratitis. In some susceptible patients, continued use of topical NSAIDs may result in epithelial breakdown, corneal thinning, corneal erosion, corneal ulceration or corneal perforation. These events may be sight threatening. Patients with evidence of corneal epithelial breakdown should immediately discontinue use of topical NSAIDs and should be closely monitored for corneal health.

Postmarketing experience with topical NSAIDs suggests that patients with complicated ocular surgeries, corneal denervation, corneal epithelial defects, diabetes mellitus, ocular surface diseases (e.g., dry eye syndrome), rheumatoid arthritis, or repeat ocular surgeries within a short period of time may be at increased risk for corneal adverse events which may become sight threatening. Topical NSAIDs should be used with caution in these patients.

Postmarketing experience with topical NSAIDs also suggests that use more than 24 hours prior to surgery or use beyond 14 days post surgery may increase patient risk for the occurrence and severity of corneal adverse events.

It is recommended that bromfenac ophthalmic solution be used with caution in patients with known bleeding tendencies or who are receiving other medications which may prolong bleeding time.

Information for Patients

Bromfenac ophthalmic solution should not be administered while wearing contact lenses.

Carcinogenesis, Mutagenesis, Impairment of Fertility

Long-term carcinogenicity studies in rats and mice given oral doses of bromfenac up to 0.6 mg/kg/day (360 times the recommended human ophthalmic dose [RHOD] of 1.67 μg/kg in 60 kg person on a mg/kg/basis, assuming 100% absorbed) and 5.0 mg/kg/day (3000 times RHOD), respectively revealed no significant increases in tumor incidence.

Bromfenac did not show mutagenic potential in various mutagenicity studies, including the reverse mutation, chromosomal aberration, and micronucleus tests.

Bromfenac did not impair fertility when administered orally to male and female rats at doses up to 0.9 mg/kg/day and 0.3 mg/kg/day, respectively (540 and 180 times RHOD, respectively).

Pregnancy

Teratogenic Effects

Pregnancy Category C

Reproduction studies performed in rats at oral doses up to 0.9 mg/kg/day (540 times RHOD) and in rabbits at oral doses up to 7.5 mg/kg/day (4500 times RHOD) revealed no evidence of teratogenicity due to bromfenac. However, 0.9mg/kg/day in rats caused embryo-fetal lethality, increased neonatal mortality, and reduced postnatal growth. Pregnant rabbits treated with 7.5 mg/kg/day caused increased post-implantation loss.

There are no adequate and well-controlled studies in pregnant women. Because animal reproduction studies are not always predictive of human response, this drug should be used during pregnancy only if the potential benefit justifies the potential risk to the fetus.

Non-Teratogenic Effects

Because of the known effects of prostaglandin biosynthesis-inhibiting drugs on the fetal cardiovascular system (closure of ductus arteriosus), the use of bromfenac ophthalmic solution during late pregnancy should be avoided.

Nursing Mothers

Caution should be exercised when bromfenac ophthalmic solution is administered to a nursing woman.

Pediatric Use

Safety and efficacy in pediatric patients below the age of 18 have not been established.

Geriatric Use

There is no evidence that the efficacy or safety profiles for bromfenac ophthalmic solution differ in patients 65 years of age and older compared to younger adult patients.

Adverse Reactions

The most commonly reported adverse experiences reported following use of bromfenac ophthalmic solution after cataract surgery include: abnormal sensation in eye, conjunctival hyperemia, eye irritation (including burning/stinging), eye pain, eye pruritus, eye redness, headache, and iritis. These events were reported in 2-7% of patients.

Clinical Practice

The following events have been identified during postmarketing use of bromfenac ophthalmic solution 0.09% in clinical practice. Because they are reported voluntarily from a population of unknown size, estimates of frequency cannot be made. The events, which have been chosen for inclusion due to either their seriousness, frequency of reporting, possible causal connection to topical bromfenac ophthalmic solution 0.09%, or a combination of these factors, include corneal erosion, corneal perforation, corneal thinning, and epithelial breakdown (see PRECAUTIONS, General).

Dosage and Administration

For the treatment of postoperative inflammation and the reduction of ocular pain in patients who have undergone cataract extraction, one drop of bromfenac ophthalmic solution should be applied to the affected eye(s) two times daily beginning 24 hours after cataract surgery and continuing through the first 2 weeks of the postoperative period.

How Supplied

Bromfenac ophthalmic solution 0.09% is supplied in a white LDPE plastic squeeze bottle with a 15 mm LDPE white dropper-tip and 15 mm polypropylene gray cap. Tamper evidence is provided with a shrink band around the closure and neck area of the package.

NDC 54868-6343-0 | 2.5 mL in 6 mL container

Storage

Store at 20ºC to 25°C (68ºF to 77°F). [See USP Controlled Room Temperature.]

Rx Only

Distributed by:
Mylan Pharmaceuticals Inc.
Morgantown, WV 26505

JULY 2010
008582
CL:BROM:R1

Additional barcode labeling by:
Physicians Total Care, Inc.
Tulsa, Oklahoma 74146

PRINCIPAL DISPLAY PANEL - 2.5 mL Bottle Carton

NDC 54868-6343-0

BROMFENAC OPHTHALMIC SOLUTION
0.09%

Sterile

Rx only

2.5 mL
For topical application in the eye